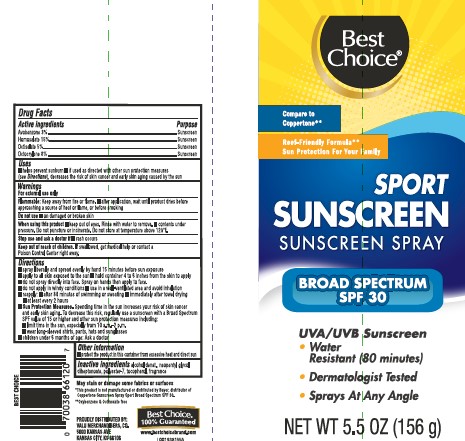 DRUG LABEL: Sunscreen
NDC: 63941-926 | Form: SPRAY
Manufacturer: Valu Merchandisers Company
Category: otc | Type: HUMAN OTC DRUG LABEL
Date: 20260216

ACTIVE INGREDIENTS: AVOBENZONE 30 mg/1 g; HOMOSALATE 150 mg/1 g; OCTISALATE 50 mg/1 g; OCTOCRYLENE 80 mg/1 g
INACTIVE INGREDIENTS: ALCOHOL; NEOPENTYL GLYCOL; NEOPENTYL GLYCOL DIHEPTANOATE; POLYESTER-7; TOCOPHEROL

Best Choice 926.000/926AA
Sport Sunscreen Spray SPF 30

Active ingredients

Avobenzone 3%

Homosalate 15%

Octisalate 5%

Octocrylene 8%

Purpose

sunscreen

Uses

- helps prevent sunburn
- if used as directed with other sun protection measures (see Directions), decreases the risk of skin cancer and early skin aging caused by the sun

Warnings

For external use only

Flammable: Keep away from fire or flame.

- after application, wait until product dries before approaching a source of heat or flame, or before smoking

When using this product

do not use in or near eyes

Do not use

on damaged or broken skin

When using this product

- keep out of eyes. Rinse with water to remove.
- contents under pressure. Do not puncture or incinerate. Do not store at temperature above 120° F.

Stop use and ask a doctor if

rash occurs

Keep out of reach of children.

If swallowed, get medical help or contact a Poison Control Center right away.

Directions

■ spray liberally and spread evenly by hand 15 minutes before sun exposure
■ apply to all skin exposed to the sun
■ hold container 4 to 6 inches from the skin to apply
■ do not spray directly into face. Spray on hands then apply to face.
■ do not apply in windy conditions
■ use in a well-ventilated area and avoid inhalation
■ reapply:
■ after 80 minutes of swimming or sweating
■ immediately after towel drying
■ at least every 2 hours
■ Sun Protection Measures.Spending time in the sun increases your risk of skin cancer and early skin aging. To decrease this risk, regularly use a sunscreen with a Broad Spectrum SPF value of 15 or higher and other sun protection measures including:
■ limit time in the sun, especially from 10 a.m.–2 p.m.
■ wear long-sleeved shirts, pants, hats and sunglasses
■ children under 6 months of age: Ask a doctor

Other information

■ protect the product in this container from excessive heat and direct sun

Inactive ingredients

alcohol denat., neopentyl glycol diheptanoate, polyester-7, tocopherol, fragrance

Disclaimers

May stain or damage some fabrics or surfaces

*This product is not manufactured or distributed by Bayer, distributor of Coppertone Sunscreen Spray Sport Broad Spectrum SPF 30.

**Oxybenzone & Octinoxate Free

ADVERSE REACTION

Best Choice

100% Guaranteed

PROUDLY DISTRIBUTED BY:

VALU MERCHANDISERS, CO.

5000 KANSAS AVE

KANSAS CITY, KS 66106

www.bestchoicebrand.com

Principal Panel Display

Best Choice®

Compare to Coppertone®*

Reef-Friendly Formula**

Sun Protection For Your Family

SPORT

SUNSCREEN

SUNSCREEN SPRAY

BROAD SPECTRUM

SPF 30

UVA/UVB Sunscreen

- Water Resistant (80 minutes)
- Dermatologist Tested
- Sprays At Any Angle

NET WT 5.5 OZ (156 g)